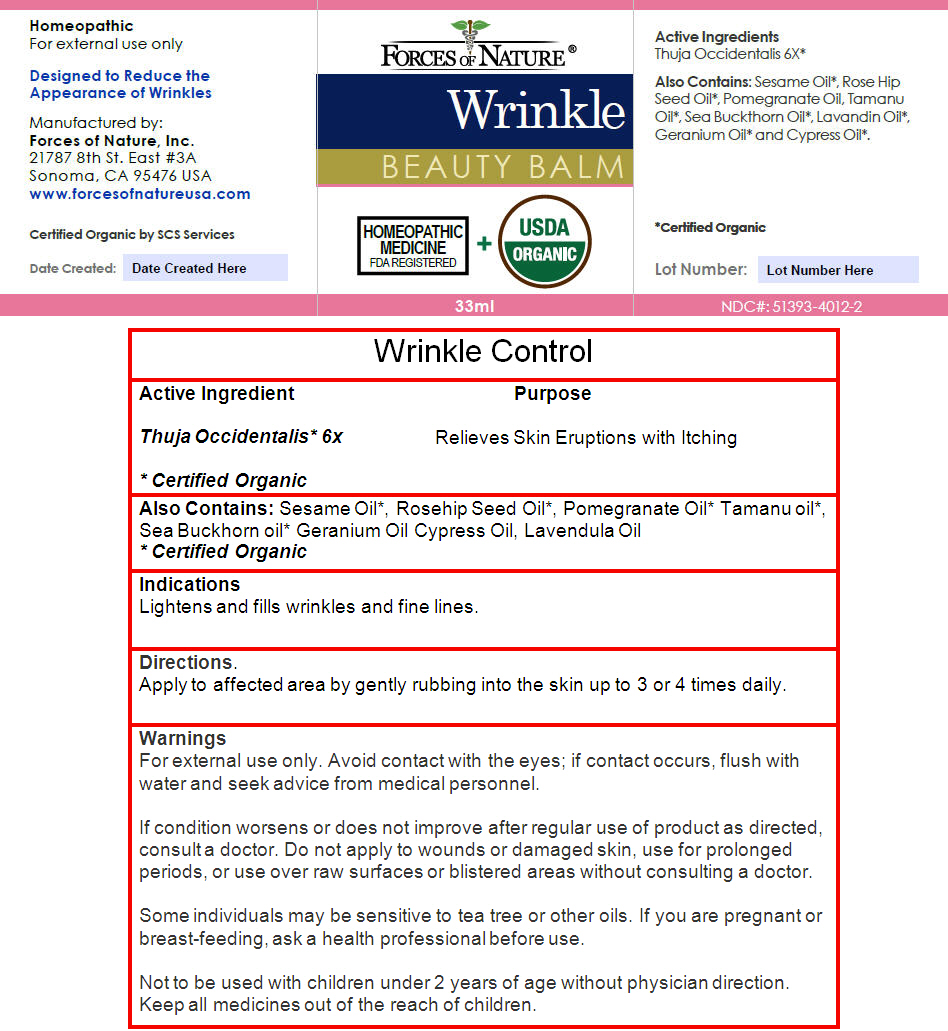 DRUG LABEL: Wrinkle Control
NDC: 51393-4012 | Form: SOLUTION/ DROPS
Manufacturer: Forces of Nature
Category: homeopathic | Type: HUMAN OTC DRUG LABEL
Date: 20140102

ACTIVE INGREDIENTS: THUJA OCCIDENTALIS LEAF 6 [hp_X]/100 mL
INACTIVE INGREDIENTS: ROSA MOSCHATA OIL; POMEGRANATE SEED OIL; Lavender Oil; PELARGONIUM GRAVEOLENS FLOWER OIL; CUPRESSUS SEMPERVIRENS LEAF OIL; Tamanu Oil; HIPPOPHAE RHAMNOIDES FRUIT OIL; Sesame Oil

Wrinkle Control

Active Ingredient

Thuja Occidentalis [Certified Organic] 6x

Purpose

Relieves Skin Eruptions with Itching

Also Contains

Sesame Oil [Certified Organic] , Rosehip Seed Oil, Pomegranate Oil Tamanu oil, Sea Buckhorn oil Geranium Oil Cypress Oil, Lavendula Oil

Indications

Lightens and fills wrinkles and fine lines.

Directions

Apply to affected area by gently rubbing into the skin up to 3 or 4 times daily.

Warnings

For external use only. Avoid contact with the eyes; if contact occurs, flush with water and seek advice from medical personnel.

ASK DOCTOR

If condition worsens or does not improve after regular use of product as directed, consult a doctor. Do not apply to wounds or damaged skin, use for prolonged periods, or use over raw surfaces or blistered areas without consulting a doctor.

Some individuals may be sensitive to tea tree or other oils.

PREGNANCY OR BREAST FEEDING

If you are pregnant or breast-feeding, ask a health professional before use.

DO NOT USE

Not to be used with children under 2 years of age without physician direction.

KEEP OUT OF REACH OF CHILDREN

Keep all medicines out of the reach of children.

Manufactured by:
Forces of Nature, Inc.
21787 8th St. East #3A
Sonoma, CA 95476 USA

PRINCIPAL DISPLAY PANEL - 33 ml Bottle Label

FORCES OF NATURE ®

Wrinkle
BEAUTY BALM

HOMEOPATHIC
MEDICINE
FDA REGISTERED
+
USDA
ORGANIC

33ml